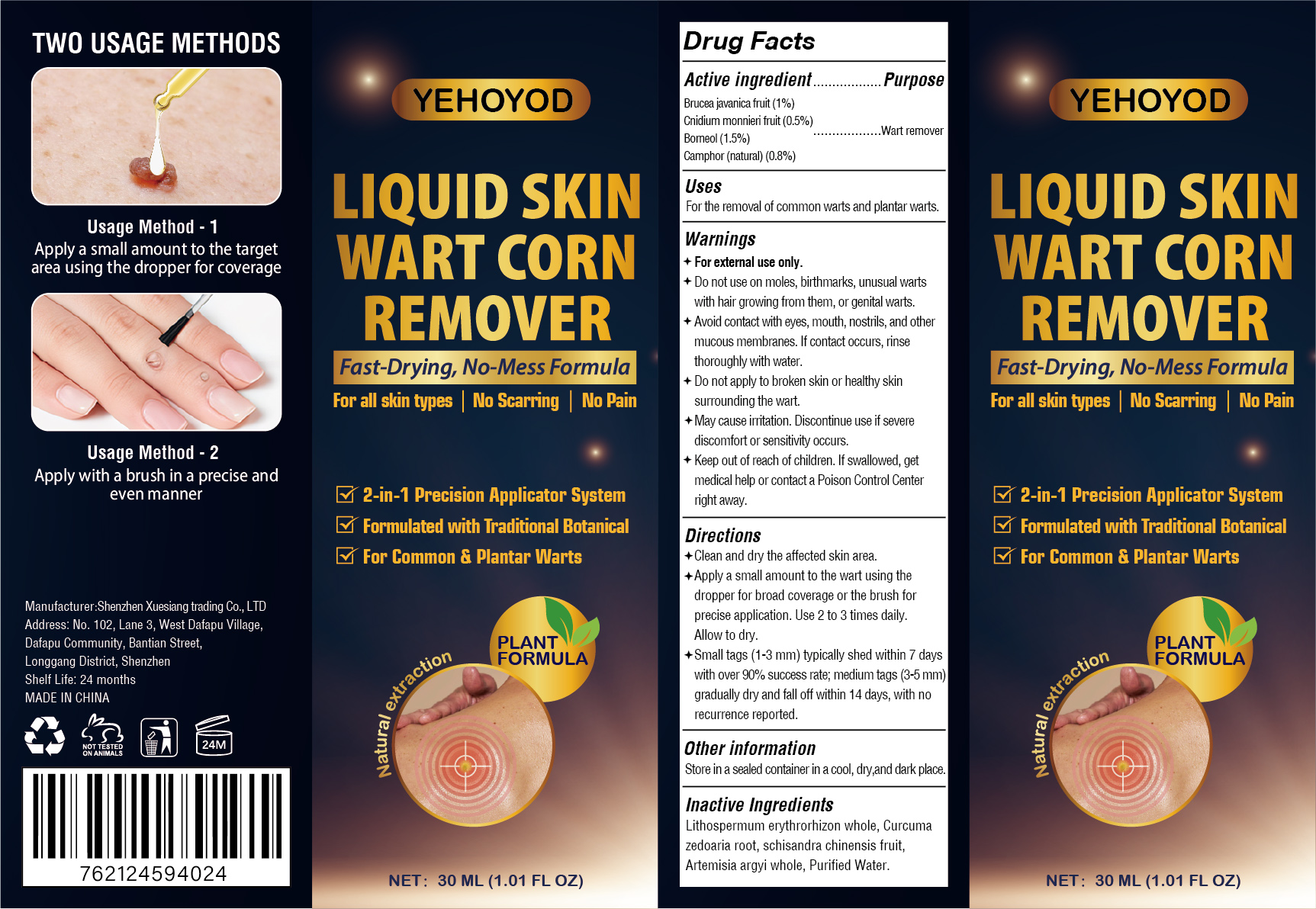 DRUG LABEL: YEHOYOD WART CORN REMOVER
NDC: 87323-001 | Form: LIQUID
Manufacturer: Shenzhen Xuesiang Trading Co., Ltd
Category: otc | Type: HUMAN OTC DRUG LABEL
Date: 20260108

ACTIVE INGREDIENTS: BORNEOL 0.015 g/1 mL; CNIDIUM MONNIERI FRUIT 0.005 g/1 mL; CAMPHOR (NATURAL) 0.008 g/1 mL; BRUCEA JAVANICA FRUIT 0.01 g/1 mL
INACTIVE INGREDIENTS: CURCUMA ZEDOARIA ROOT; SCHISANDRA CHINENSIS FRUIT; ARTEMISIA ARGYI WHOLE; LITHOSPERMUM ERYTHRORHIZON WHOLE; WATER

87323-001 YEHOYOD WART CORN REMOVER

ACTIVE INGREDIENT

Brucea javanica fruit 1%
Cnidium monnieri fruit 0.5%
Borneol 1.5%
Camphor(natural) 0.8%

PURPOSE

Wart remover

INDICATIONS AND USAGE

For the removal of common warts and plantar warts.

WARNINGS

For external use only.

Do not use on moles, birthmarks, unusual wartswith hair growing from them, or genital warts.
Do not apply to broken skin or healthy skinsurrounding the wart.

WHEN USING

Avoid contact with eyes, mouth, nostrils, and other mucous membranes. lf contact occurs, rinse thoroughly with water.

STOP USE

May cause irritation. Discontinue use if severediscomfort or sensitivity occurs.

Keep out of reach of children. lf swallowed, get medical help or contact a Poison Control Center right away.

DOSAGE AND ADMINISTRATION

Clean and dry the affected skin area.
Apply a small amount to the wart using the dropper for broad coverage or the brush for precise application. Use 2 to 3 times daily.Allow to dry.
Small tags (1-3 mm) typically shed within 7 days with over 90% success rate; medium tags (3-5 mm) gradually dry and fall off within 14 days, with no recurrence reported.

INACTIVE INGREDIENT

Lithospermum erythrorhizon whole
Curcuma zedoaria root
schisandra chinensis fruit
Artemisia argyi whole
Purified Water